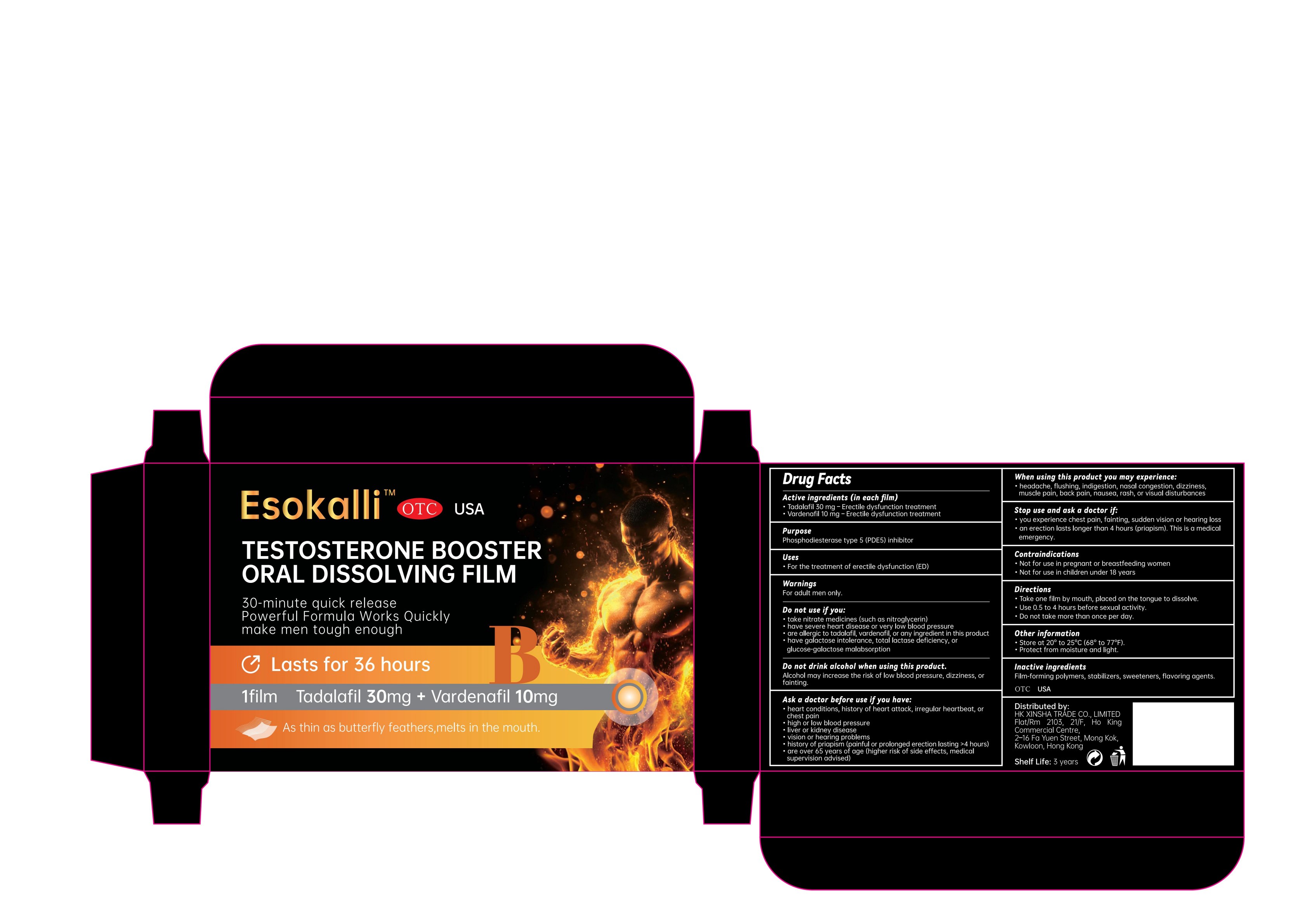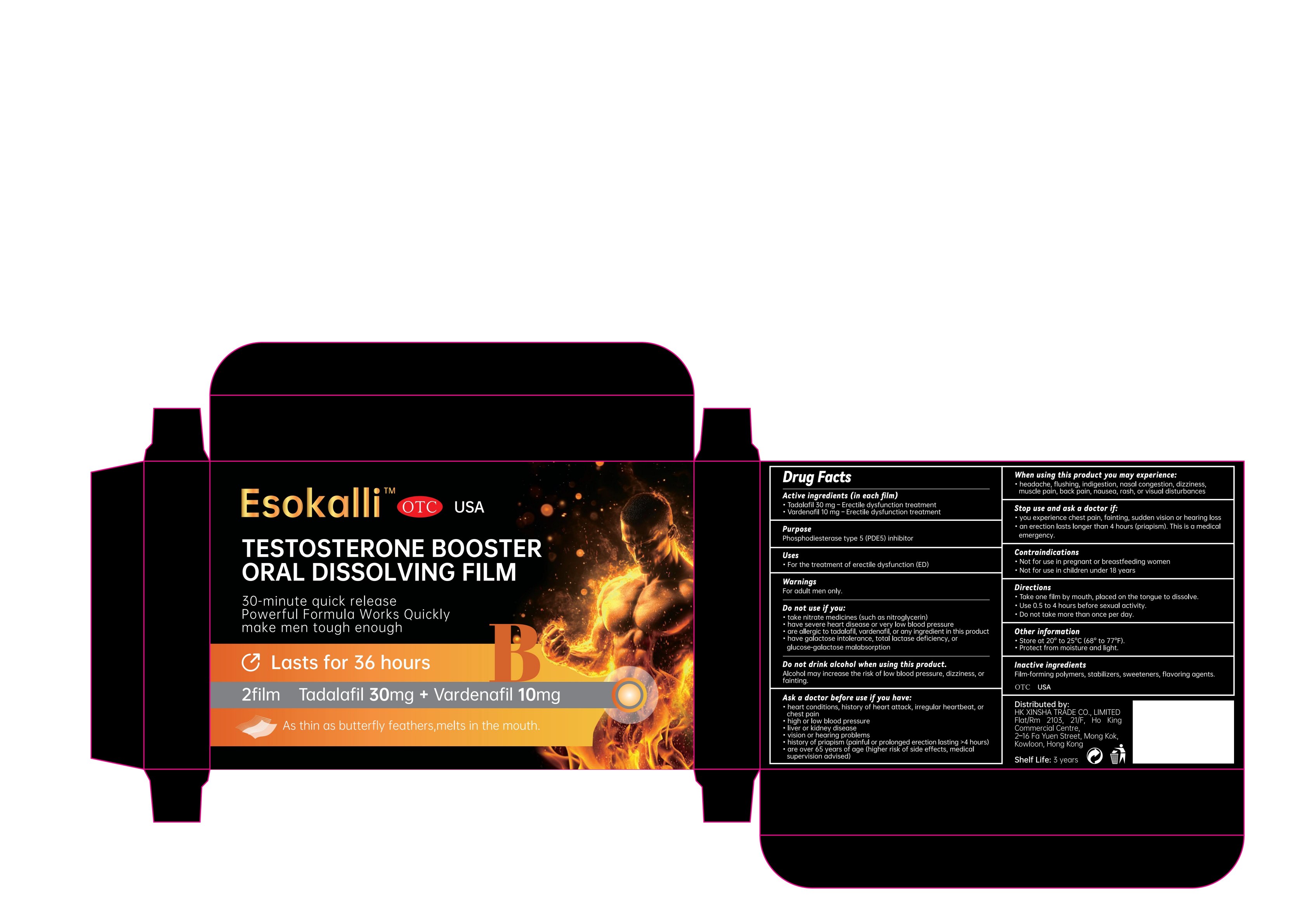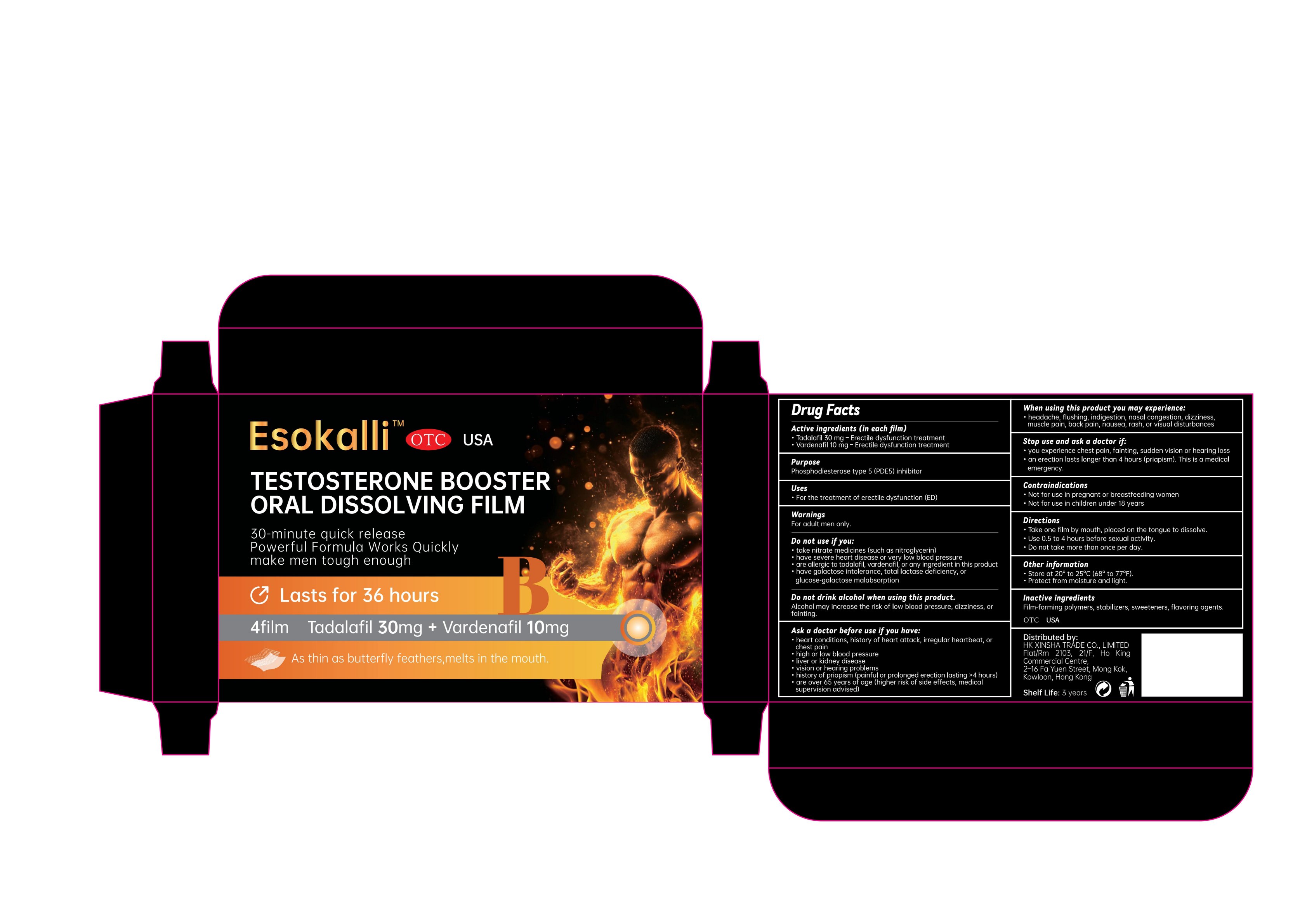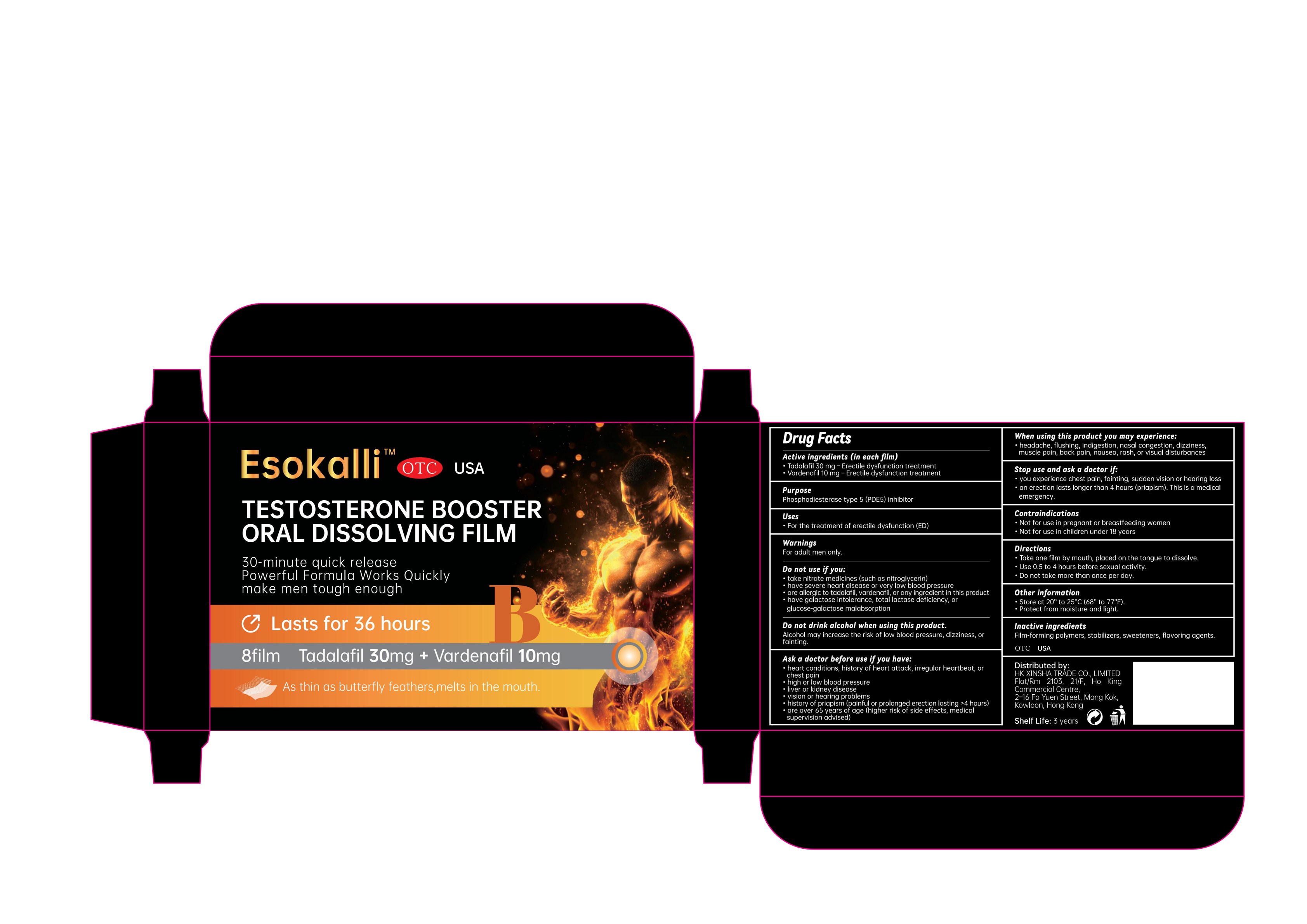 DRUG LABEL: Esokalli Testosterone Booster Oral Dissolving Film
NDC: 84778-092 | Form: FILM, SOLUBLE
Manufacturer: Guangzhou Yixin Cross-border E-commerce Co., Ltd.
Category: otc | Type: HUMAN OTC DRUG LABEL
Date: 20251219

ACTIVE INGREDIENTS: VARDENAFIL 10 mg/100 mg; TADALAFIL 30 mg/100 mg
INACTIVE INGREDIENTS: HYPROMELLOSES; SUCRALOSE; SUCROSE

Active ingredients (in each film)

Tadalafil 30 mg – Erectile dysfunction treatment
Vardenafil 10 mg – Erectile dysfunction treatment

Purpose

Phosphodiesterase type 5 (PDE5) inhibitors

Uses

For the treatment of erectile dysfunction (ED)

Warnings

For adult men only.

Do not use if you:

take nitrate medicines (such as nitroglycerin)
have severe heart disease or very low blood pressure
are allergic to tadalafil, vardenafil, or any ingredient in this product
have galactose intolerance, total lactase deficiency, or glucose-galactose malabsorption

Dosage and administration

• Take 1 oral film as a single dose.
• Administer orally by placing on the tongue until dissolved.
• Administer approximately 0.5 to 4 hours prior to anticipated sexual activity.
• Do not exceed 1 dose in 24 hours.

When using this product you may experience:

headache, flushing, indigestion, nasal congestion, dizziness, muscle pain, back pain, nausea, rash, or visual disturbances

Stop use and ask a doctor if:

you experience chest pain, fainting, sudden vision or hearing loss
an erection lasts longer than 4 hours (priapism). This is a medical emergency.

Contraindications

Not for use in pregnant or breastfeeding women
Not for use in children under 18 years

Inactive ingredients

Film-forming polymers, stabilizers, sweeteners, flavoring agents.